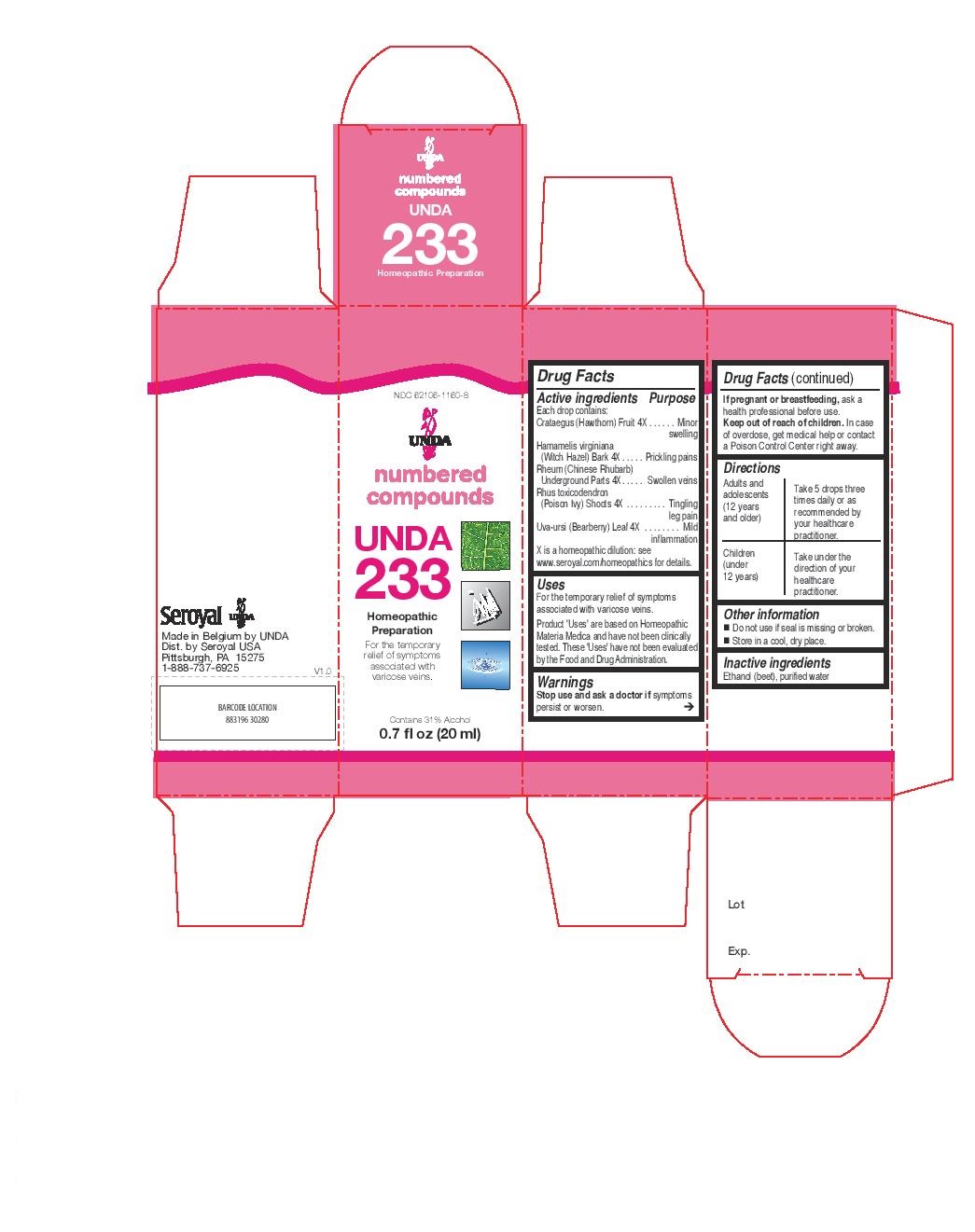 DRUG LABEL: Unda 233
NDC: 62106-1160 | Form: LIQUID
Manufacturer: Seroyal USA
Category: homeopathic | Type: HUMAN OTC DRUG LABEL
Date: 20221109

ACTIVE INGREDIENTS: RHEUM TANGUTICUM WHOLE 4 [hp_X]/20 mL; HAWTHORN LEAF WITH FLOWER 4 [hp_X]/20 mL; ARCTOSTAPHYLOS UVA-URSI LEAF 4 [hp_X]/20 mL; TOXICODENDRON PUBESCENS LEAF 4 [hp_X]/20 mL; HAMAMELIS VIRGINIANA ROOT BARK/STEM BARK 4 [hp_X]/20 mL
INACTIVE INGREDIENTS: ALCOHOL; WATER

Unda 233

Active ingredients
Each drop contains:
Crataegus (Hawthorn) Fruit 4X
Hamamelis virginiana (Witch Hazel) Bark 4X
Rheum (Chinese Rhubarb) Underground Parts 4X.
Rhus toxicodendron (Poison Ivy) Shoots 4X
Uva-ursi (Bearberry) Leaf 4X

Uses
For the temporary relief of symptoms
associated with varicose veins.

Warnings

Stop use and ask a doctor if symptoms persist or worsen.

If pregnant or breastfeeding, ask a health professional before use.

Keep out of reach of children.

In case of overdose, get medical help or contact a
Poison Control Center right away.

PREGNANCY OR BREAST FEEDING

If pregnant or breastfeeding, ask a health professional before use.

Keep out of reach of children.

OVERDOSAGE

In case of overdose, get medical help or contact a
Poison Control Center right away.

Inactive Ingredients:

Ethanol (beet),
purified water

Directions
Adults and adolescents (12 years and older)

Take 5 drops three times daily or as recommended by your healthcare practitioner.

Children (under 12 years)

Take under the direction of your healthcare practitioner.

Uses
For the temporary relief of symptoms
associated with varicose vein problems.

Directions
Adults and adolescents (12 years and older)

Take 5 drops three times daily or as recommended by your healthcare practitioner.

Children (under 12 years)

Take under the direction of your healthcare practitioner.

Other information
Do not use if seal is missing or broken.
Store in a cool, dry place.

PACKAGE LABEL

NDC 62106-1160-8

UNDA

numbered compounds

UNDA 233

Homeopathic Preparation

Contains 31% Alcohol
0.7 fl oz (20 ml)